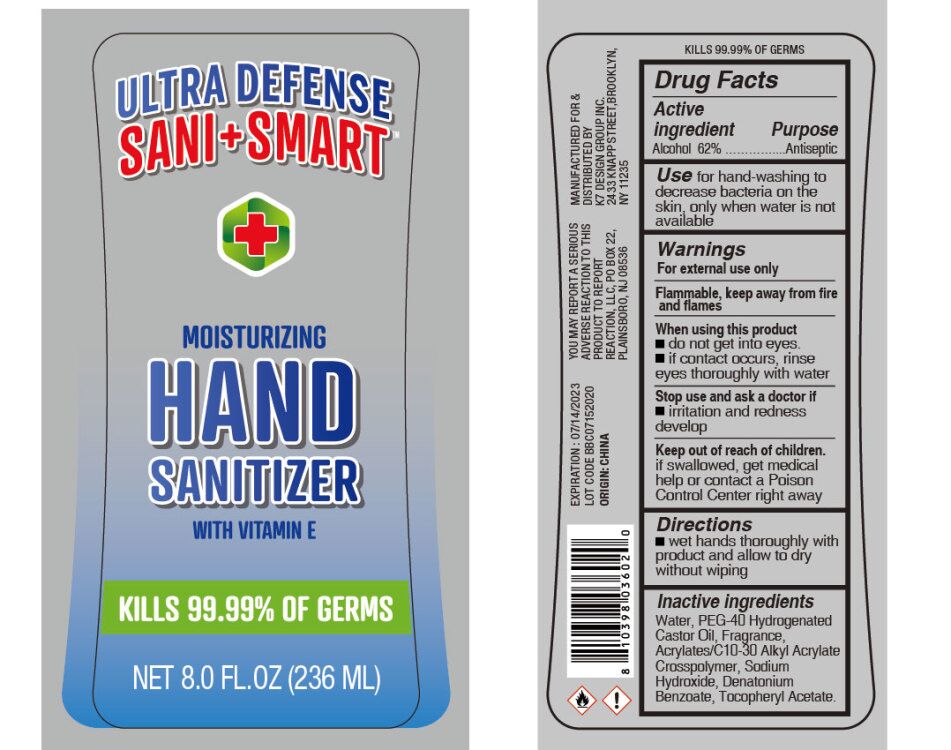 DRUG LABEL: Hand Sanitizer
NDC: 74177-027 | Form: LIQUID
Manufacturer: K7 Design Group Inc.
Category: otc | Type: HUMAN OTC DRUG LABEL
Date: 20200911

ACTIVE INGREDIENTS: ALCOHOL 62 mL/100 mL
INACTIVE INGREDIENTS: .ALPHA.-TOCOPHEROL ACETATE; DENATONIUM BENZOATE; WATER; CARBOMER INTERPOLYMER TYPE A (55000 CPS); POLYOXYL 40 HYDROGENATED CASTOR OIL; SODIUM HYDROXIDE

K7 BBC Hand Sanitizer with VitE

Active ingredient

Alcohol 62%

Purpose

Antiseptic

Use

for hand washing to decrease bacteria on the skin, only when water is not available

Warnings

For external use only. Flammable, keep away from fire and flames

When using this product

■ do not get into eyes. ■ if contact occurs, rinse eyes thoroughly with water

Stop use and ask a doctor if

■ irritation and redness develop

Keep out of reach of children

if swallowed, get medical help or contact a Poison Control Center right away.

Directions

■ wet hands thoroughly with product and allow to dry without wiping

Inactive ingredients

Water, PEG-40 Hydrogenated Castor Oil, Fragrance, Acrylates/C10-30 Alkyl Acrylate Crosspolymer, Sodium Hydroxide, Denatonium Benzoate, Tocopheryl Acetate